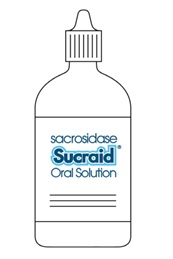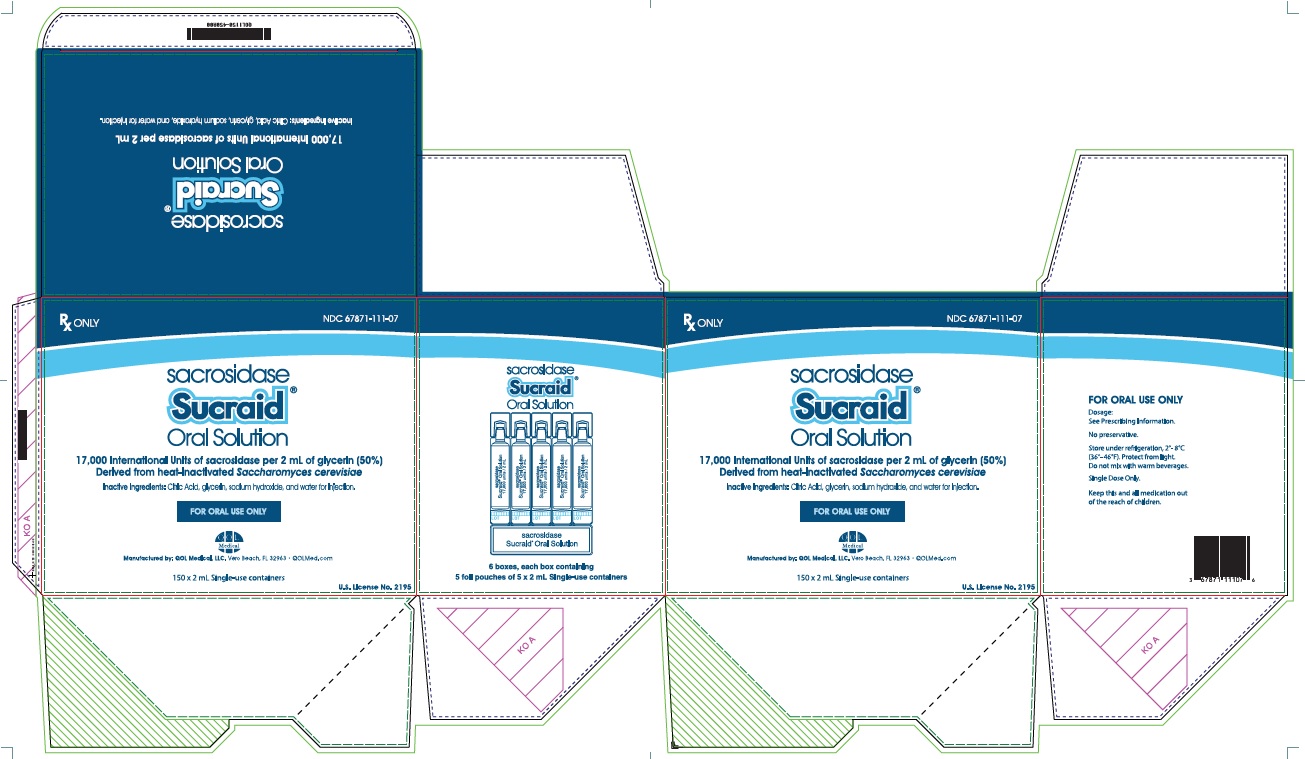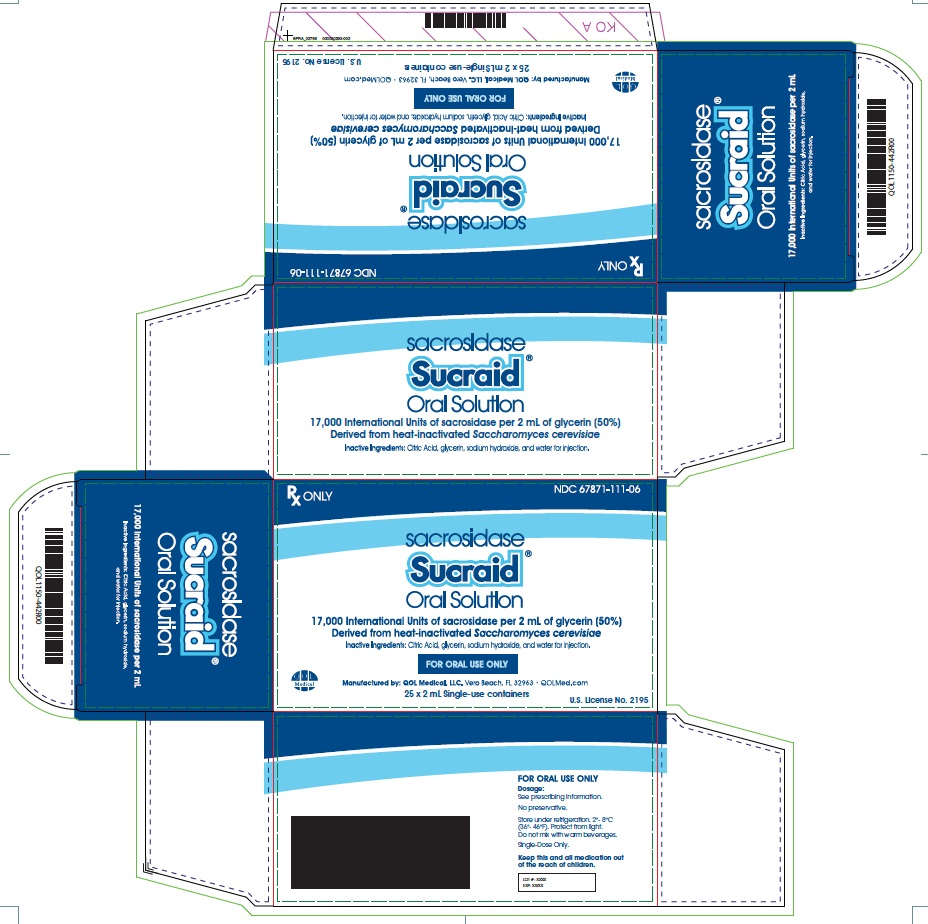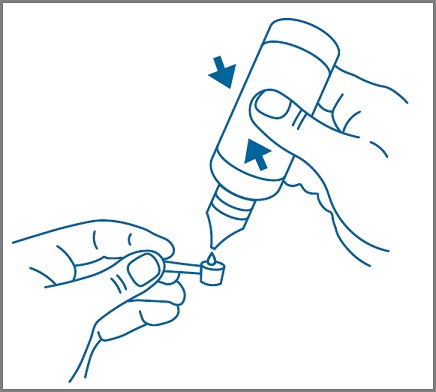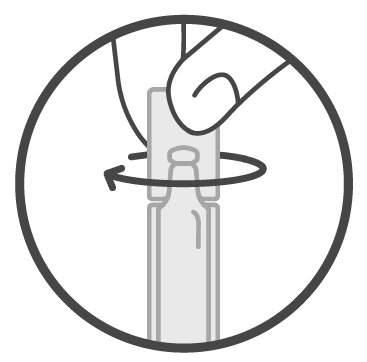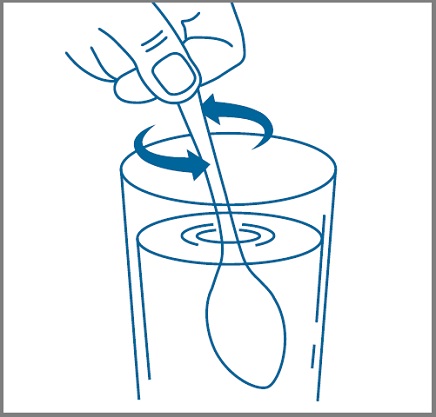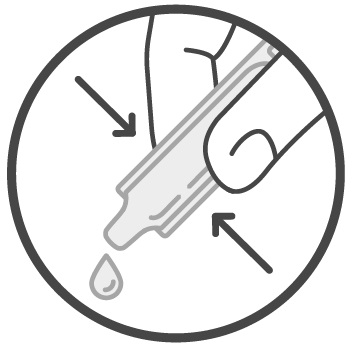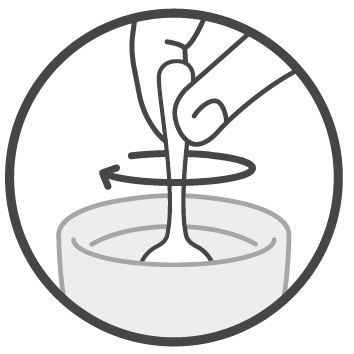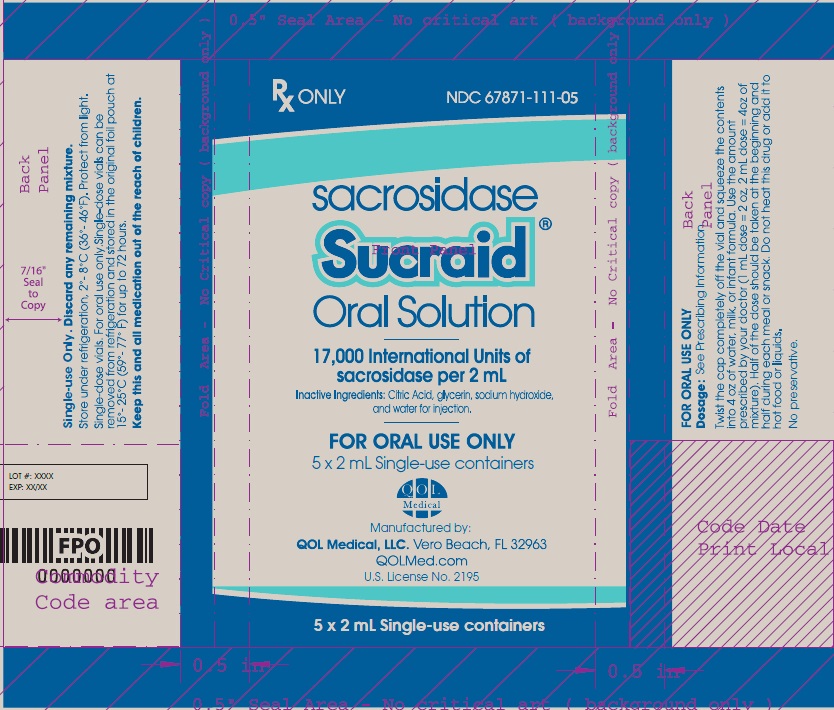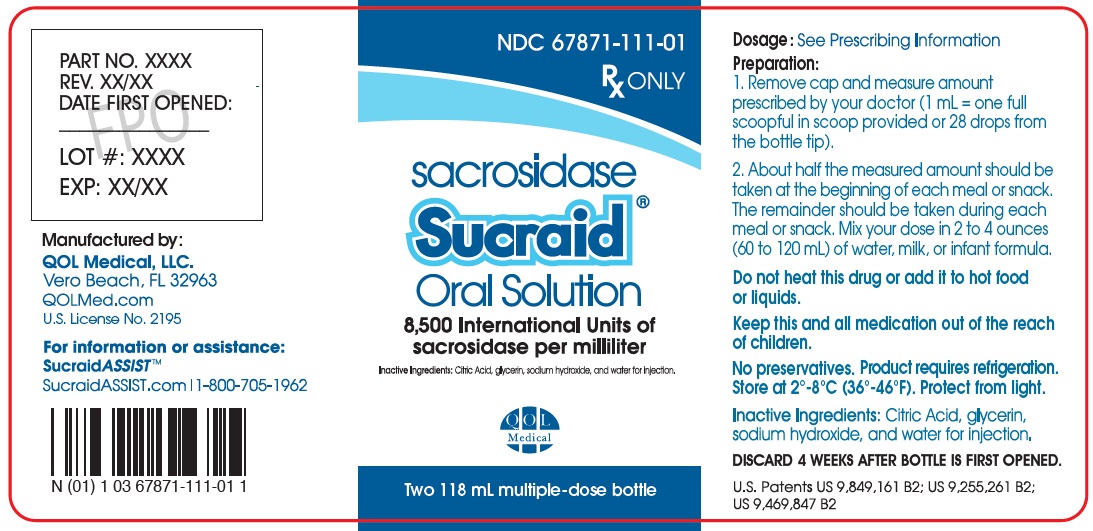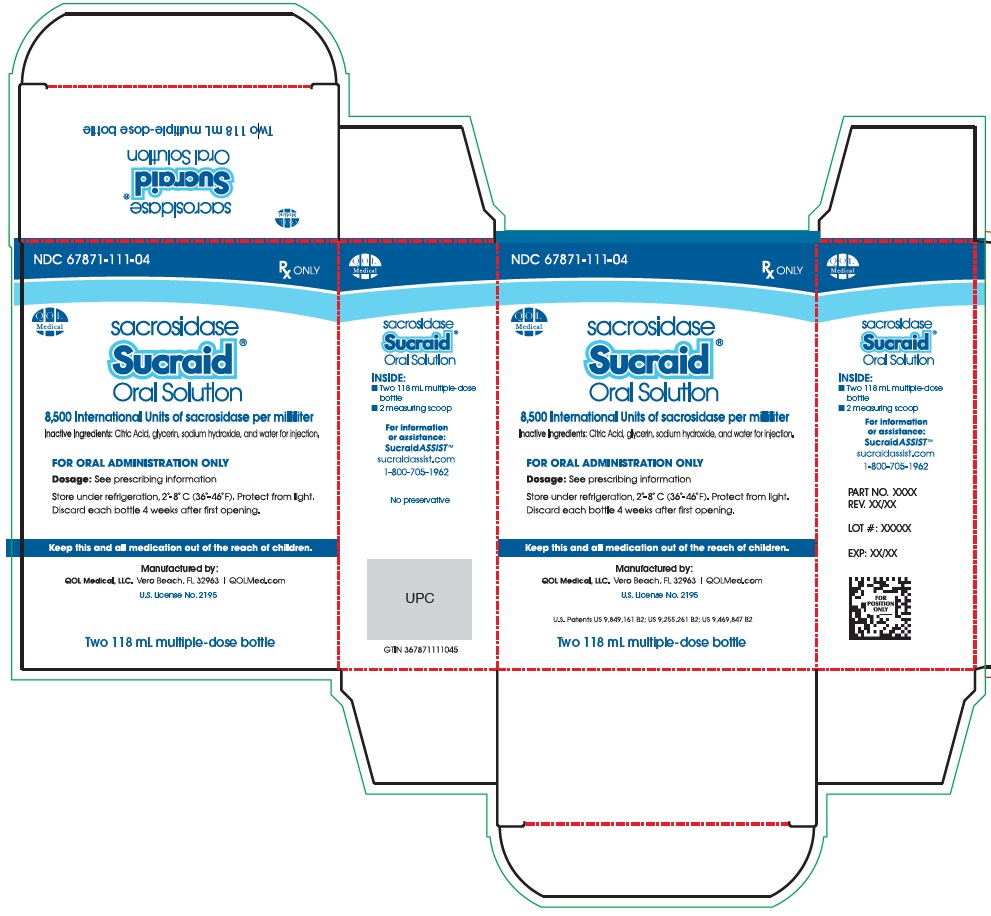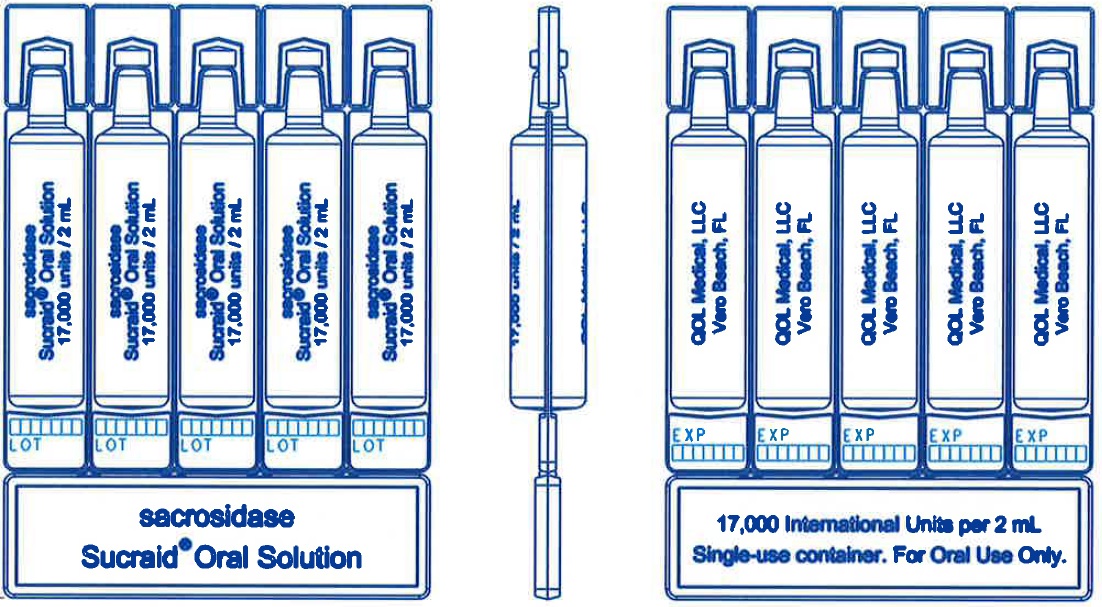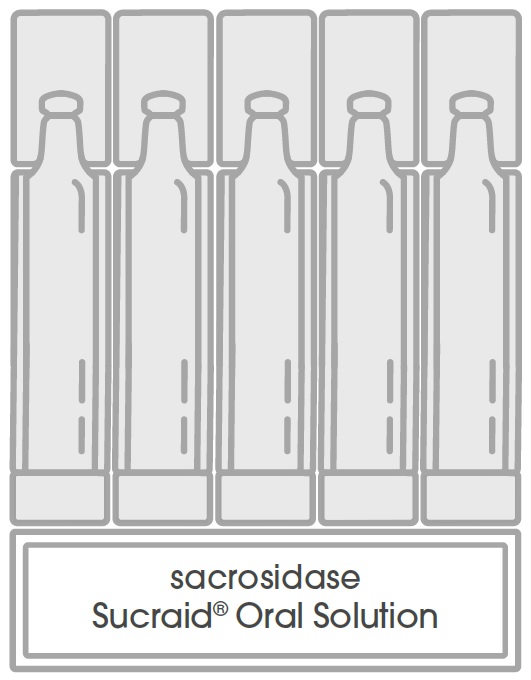 DRUG LABEL: Sucraid
NDC: 67871-111 | Form: SOLUTION
Manufacturer: QOL Medical, LLC
Category: prescription | Type: HUMAN PRESCRIPTION DRUG LABEL
Date: 20251229

ACTIVE INGREDIENTS: SACROSIDASE 8500 [iU]/1 mL
INACTIVE INGREDIENTS: GLYCERIN; WATER; ANHYDROUS CITRIC ACID; SODIUM HYDROXIDE

Sucraid® (sacrosidase) Oral Solution:

DESCRIPTION

Sacrosidase is an enzyme with the chemical name of β,D-fructofuranoside fructohydrolase. The enzyme is derived from baker’s yeast (Saccharomyces cerevisiae). It has been reported that the primary amino acid structure of this protein consists of 513 amino acids with an apparent molecular weight of 100,000 Da for the glycosylated monomer (range 66,000- 116,000 Da). Reports also suggest that the protein exists in solution as a monomer, dimer, tetramer, and octomer ranging from 100,000 Da to 800,000 Da. It has an isoelectric point (pI) of 4.5.

Sucraid®(sacrosidase) Oral Solution is an oral enzyme replacement therapy.

Sucraid is a pale yellow to colorless, clear solution with a pleasant, sweet taste. Each milliliter (mL) of Sucraid contains 8,500 International Units (I.U.) of the enzyme sacrosidase, the active ingredient.

Sucraid may contain small amounts of papain (see WARNINGS). Papain is a protein-cleaving enzyme that is introduced in the manufacturing process to digest the cell wall of the yeast and may not be completely removed during subsequent process steps. Sucraid contains sacrosidase in a vehicle comprised of glycerin, water, citric acid, and sodium hydroxide to maintain the pH at 4.0 to 4.7. Glycerol (glycerin) in the amount consumed in the recommended doses of Sucraid has no expected toxicity.

This enzyme preparation is fully soluble with water, milk, and infant formula. DO NOT HEAT SOLUTIONS CONTAINING SUCRAID. Do not put Sucraid in warm or hot liquids (see DOSAGE AND ADMINISTRATION, Administration Instructions).

CLINICAL PHARMACOLOGY

Congenital sucrase-isomaltase deficiency (CSID) is a chronic, autosomal recessive, inherited, phenotypically heterogeneous disease with very variable enzyme activity. CSID is usually characterized by a complete or almost complete lack of endogenous sucrase activity, a very marked reduction in isomaltase activity, and a moderate decrease in maltase activity.

Sucrase is naturally produced in the brush border of the small intestine, primarily the distal duodenum and jejunum. Sucrase hydrolyzes the disaccharide sucrose into its component monosaccharides, glucose and fructose. Isomaltase breaks down disaccharides from starch into simple sugars. Sucraid does not contain isomaltase.

In the absence of endogenous human sucrase, as in CSID, sucrose is not metabolized. Unhydrolyzed sucrose and starch are not absorbed from the intestine and their presence in the intestinal lumen may lead to osmotic retention of water. This may result in loose stools.

Unabsorbed sucrose in the colon is fermented by bacterial flora to produce increased amounts of hydrogen, methane, and water. As a consequence, excessive gas, bloating, abdominal cramps, diarrhea, nausea, and vomiting may occur.

Chronic malabsorption of disaccharides may result in malnutrition. Undiagnosed/untreated CSID patients often fail to thrive and fall behind in their expected growth and development curves. Previously, the treatment of CSID has required the continual use of a strict sucrose-free diet.

CLINICAL STUDIES

A two-phase (dose response preceded by a breath hydrogen phase) double-blind, multi-site, crossover trial was conducted in 28 pediatric patients (approximately 5 months to 12 years of age) with confirmed CSID. During the dose response phase, the patients were challenged with an ordinary sucrose-containing diet while receiving each of four doses of sacrosidase: full strength (9000 I.U./mL) and three dilutions (1:10 [900 I.U./mL], 1:100 [90 I.U./mL], and 1:1000 [9 I.U./mL]) in random order for a period of 10 days. Patients who weighed no more than 15 kg received 1 mL per meal; those weighing more than 15 kg received 2 mL per meal. The dose did not vary with age or sucrose intake. A dose-response relationship was shown between the two higher and the two lower doses. The two higher doses of sacrosidase were associated with significantly fewer total stools and higher proportions of patients having lower total symptom scores, the primary efficacy end-points. In addition, higher doses of sacrosidase were associated with a significantly greater number of hard and formed stools as well as with fewer watery and soft stools, the secondary efficacy end-points.

Analysis of the overall symptomatic response as a function of age indicated that in CSID pediatric patients up to 3 years of age, 86% became asymptomatic. In pediatric patients over 3 years of age, 77% became asymptomatic. Thus, the therapeutic response did not differ significantly according to pediatric age.

A second study of similar design and execution as the first used 4 different dilutions of sacrosidase: 1:100 (90 I.U./mL), 1:1000 (9 I.U./mL), 1:10,000 (0.9 I.U./mL), and 1:100,000 (0.09 I.U./mL). There were inconsistent results with regards to the primary efficacy parameters.

In both trials, however, pediatric patients showed a marked decrease in breath hydrogen output when they received sacrosidase in comparison to placebo.

The effects of Sucraid have not been evaluated in patients with secondary (acquired) sucrase deficiency.

INDICATIONS AND USAGE

Sucraid® (sacrosidase) Oral Solution is indicated for the treatment of sucrase deficiency, which is part of congenital sucrase-isomaltase deficiency (CSID), in adult and pediatric patients 5 months of age and older.

CONTRAINDICATIONS

Sucraid is contraindicated in patients known to be hypersensitive to yeast, yeast products, glycerin (glycerol), or papain (see WARNINGS).

WARNINGS

Severe Hypersensitivity Reactions

Severe hypersensitivity reactions, including wheezing, rash, and pruritis, have been reported with administration of Sucraid. Sucraid contains papain, which is associated with hypersensitivity reactions (see DESCRIPTION).

A pediatric patient in the clinical trials experienced a hypersensitivity reaction of severe wheezing that required hospitalization. Postmarketing cases of cutaneous hypersensitivity reactions have also been reported.

Instruct patients or caregivers to stop Sucraid and seek medical attention if symptoms suggestive of a hypersensitivity reaction occur. Sucraid is contraindicated in patients who have had a known hypersensitivity reaction (see CONTRAINDICATIONS).

PRECAUTIONS

Increased Blood Glucose Concentrations in Patients with Diabetes Mellitus

Sucraid enables the products of sucrose hydrolysis, glucose and fructose, to be absorbed and may increase blood glucose concentrations. Monitor blood glucose concentrations and adjust the diet accordingly for patients with diabetes mellitus.

Dietary Starch Restriction

Sucraid does not replace isomaltase. Therefore, patients may still experience symptoms of CSID while taking Sucraid. Consider dietary starch restriction in addition to Sucraid, especially in patients in whom symptoms are not adequately controlled by Sucraid.

Information for Patients

See Patient Package Insert and the Instructions for Use.

Drug Interactions

Fruit Juice

The acidity in fruit juice may reduce the enzyme activity in Sucraid. Administration of Sucraid with liquids other than water, milk, or infant formula has not been studied and is not recommended (see DOSAGE AND ADMINISTRATION, Administration Instructions).

Carcinogenesis, Mutagenesis, Impairment of Fertility

Long-term studies in animals with Sucraid have not been performed to evaluate the carcinogenic potential. Studies to evaluate the effect of Sucraid on fertility or its mutagenic potential have not been performed.

Pregnancy

Teratogenic Effects

Animal reproduction studies have not been conducted with Sucraid. Sucraid is not expected to cause fetal harm when administered to a pregnant woman or to affect reproductive capacity. Sucraid should be given to a pregnant woman only if clearly needed.

Nursing Mothers

The Sucraid enzyme is broken down in the stomach and intestines, and the component amino acids and peptides are then absorbed as nutrients.

Pediatric Use

The safety and effectiveness of Sucraid for the treatment of sucrase deficiency, which is part of congenital sucrase-isomaltase deficiency (CSID), have been established in pediatric patients aged 5 months and older. Use of Sucraid for this indication is supported by evidence from adequate and well-controlled studies in pediatric patients (see CLINICAL STUDIES and ADVERSE REACTIONS).

Geriatric Use

Clinical trials of Sucraid did not include patients 65 years of age and older to determine if they respond differently from younger adult patients.

ADVERSE REACTIONS

The following adverse reactions associated with the use of sacrosidase were identified in clinical studies or postmarketing reports. Because some of these reactions were reported voluntarily from a population of uncertain size, it is not always possible to reliably estimate their frequency or establish a causal relationship to drug exposure.

In clinical studies of up to 54 months duration, a total of 52 patients were treated with Sucraid. The reported adverse reactions (number of patients) were as follows: abdominal pain (4), vomiting (3), nausea (2), diarrhea (2), constipation (2), insomnia (1), headache (1), nervousness (1), and dehydration (1).

Hypersensitivity reactions (wheezing, rash, and pruritis) have been reported (see WARNINGS).

DOSAGE AND ADMINISTRATION

Important Administration Information

- Administer Sucraid with each meal or snack.
- Mix Sucraid with cold or room temperature water, milk or infant formula prior to administration. Administration of Sucraid in liquids other than water, milk, or infant formula has not been studied and is not recommended. Do not mix or consume Sucraid with fruit juice.
- Do not warm or heat the water, milk, or infant formula before or after addition of Sucraid.
- Administer half of the dose at the beginning of the meal or snack and the other half of the dose during the meal or snack.

Recommended Dosage
The recommended dosage is:

- Patients weighing 15 kg and less:8,500 International Units (1 mL) administered orally with each meal or snack.
- Patients weighing more than 15 kg:17,000 International Units (2 mL) administered orally with each meal or snack.

Preparation and Administration Instructions for Patients Weighing 15 kg or Less
Multiple-Dose Bottle:

1. Using the measuring scoop provided, add 1 scoop of Sucraid (1 mL) to 60 mL of cold or room temperature water, milk, or infant formula.
2. Stir to mix well.
3. Administer half of the mixed Sucraid solution (30 mL) at the beginning of the meal or snack and the other half of the mixed solution (30 mL) during the meal or snack.
4. Do not save any of the mixed Sucraid solution for later use.
5. Rinse the measuring scoop with water.

Single-Use Container:

1. Empty the entire contents of the single-use container (2 mL) in 120 mL of cold or room temperature water, milk, or infant formula.
2. Stir to mix well.
3. Divide the mixed Sucraid solution into two separate 60 mL portions. The first portion (60 mL) is for immediate use.
  • Administer half of the first portion (30 mL) of the mixed Sucraid solution at the beginning of the meal or snack and the other half of the first portion (30 mL) of the mixed Sucraid solution during the meal or snack.
4. Store the second portion of the mixed Sucraid solution (60 mL) at 2°C to 8°C (36°F to 46°F) for up to 24 hours for administration with the next meal or snack.
  • Discard the mixed Sucraid solution if not used within 24 hours.

Preparation and Administration Instructions for Patients Weighing More than 15 kg
Multiple-Dose Bottle:

1. Using the measuring scoop provided, add 2 scoops of Sucraid (2 mL) to 120 mL of cold or room temperature water, milk, or infant formula.
2. Stir to mix well.
3. Administer half of the mixed Sucraid solution (60 mL) at the beginning of the meal or snack and the other half of the mixed Sucraid solution (60 mL) during the meal or snack.
4. Do not save any of the mixed Sucraid solution for later use.
5. Rinse the measuring scoop with water.

Single-Use Container:

1. Empty the entire contents of the single-use container (2 mL) in 120 mL of cold or room temperature water, milk, or infant formula.
2. Stir to mix well.
3. Administer half of the mixed Sucraid solution (60 mL) at the beginning of the meal or snack and the other half of the mixed solution during the meal or snack (60 mL).
4. Do not save any of the mixed Sucraid solution for later use.

HOW SUPPLIED

118 mL Multiple-Dose Bottle

Sucraid (sacrosidase) Oral Solution is available in 118 mL (4 fluid ounces) multiple-dose translucent plastic bottles, packaged two bottles per carton. Each mL of solution contains 8,500 International Units of sacrosidase. A 1 mL measuring scoop is provided with each bottle. A full measuring scoop is 1 mL.

NDC# 67871-111-04 (2 x 118 mL multiple-dose bottles)

Store under refrigeration at 2°C to 8°C (36°F to 46°F). Discard four weeks after first opening due to the potential for bacterial growth. Protect from heat and light.

2 mL Single-Use Container

Sucraid (sacrosidase) Oral Solution is available in 2 mL, single-use containers that are packaged into a foil pouch. Each 2 mL single-use container contains 17,000 International Units of sacrosidase. Each foil pouch holds a card of 5 containers. Five pouches are then packaged in a box (25 containers). Six boxes are further packaged in a carton (150 containers).

NDC# 67871-111-07 (150 x 2 mL single-use containers)

Store under refrigeration, 2°C to 8°C (36°F to 46°F). Protect from light. Single-use container can be removed from refrigeration and stored at 15°C to 25°C (59°F to 77°F) for up to 3 days (72 hours).

Manufactured by:
QOL Medical, LLC Vero Beach, FL 32963
U.S. License No. 2195

www.sucraid.com
For questions call 1-866-469-3773

Rev <08/24>

Instructions for Use

Sucraid® (Su-kreid) (sacrosidase) Oral Solution:

2-mL Single-Use Container

Read this Instructions for Use before you start taking or giving Sucraid to a child, and each time you get a refill. There may be new information. This information does not take the place of talking to your healthcare provider about your or your child’s medical condition or treatment.

Important information you need to know before taking or giving Sucraid:

- The 2-mL single-use container is for children and adults.
- Sucraid is supplied in 2-mL single-use containers in a foil pouch. Each foil pouch holds 5 single-use containers.

Each container is one 2 mL Sucraid dose.

- Your healthcare provider will decide the right dose of Sucraid for you or your child. Do notchange the dose of Sucraid without talking to your healthcare provider.
- Sucraid can only be dissolved with cold or room temperature water, milk, or infant formula. Do notput Sucraid in warm or hot liquids. Do notdissolve Sucraid with fruit juice. Do notgive or take Sucraid with fruit juice.
- Do notwarm or heat the mixed solution before taking or giving Sucraid.
- Sucraid should be taken or given with each meal or snack. Half of the Sucraid dose should be taken at the beginning of each meal or snack. Take or give the remaining Sucraid dose during the meal or snack.
- Do notuse the Sucraid single-use container if the seal has been damaged. Contact your pharmacist or healthcare provider if you cannot use the Sucraid single-use container.

Supplies needed to take or give Sucraid:

- 1 Sucraid 2-mL container
- 4 ounces of cold or room temperature water, milk, or infant formula (not included)
- Meal or snack (not included)
- Spoon to mix (not included)

How to take or give Sucraid:

Step 1:Check the expiration date on the Sucraid foil pouch. Do notuse Sucraid if it is past the expiration date.
Remove 1 Sucraid 2-mL container from a foil pouch.

Step 2:Twist the cap to the left to remove it from the container. See Figure 1.

.

Figure 1

Step 3: Squeeze all the Sucraid solution in the container into 4 ounces of cold or room temperature water, milk, or infant formula. See Figure 2.

Figure 2

Step 4: Mix your or your child’s prescribed dose in 4 ounces of cold or room temperature water, milk, or infant formula.
See Figure 3.

Figure 3

Step 5:
For patients weighing more than 33 pounds (15 kilograms):

- The entire 4 ounces of mixed solution will be taken or given during each meal or snack. Take or give half of the mixed solution (2 ounces) at the beginning of the meal or snack and take or give the other half of the mixed solution (2 ounces) during the meal or snack.

For patients weighing 33 pounds (15 kilograms) or less:

- Divide the 4-ounce mixed solution into two separate 2-ounce portions.
- Take or give half of the first portion (1 ounce) at the beginning of the meal or snack and take or give the other half of the first portion (1 ounce) during the meal or snack.
- Store the second portion (2 ounces) in the refrigerator at 36°F to 46°F (2°C to 8°C) for the next meal or snack. Take or give half of the second portion (1 ounce) at the beginning of the next meal or snack and take or give the other half of the second portion (1 ounce) during the meal or snack.
- Throw away the second portion (2 ounces) if you do not use it within 24 hours.

Throwing away (disposal of) Sucraid:

- Throw away expired or empty Sucraid containers in your household trash.

How should I store Sucraid?

• Store the Sucraid single-use container in the refrigerator between 36°F to 46°F (2°C to 8°C).

• The Sucraid single-use container may be stored between 59°F to 77°F (15°C to 25°C) for up to 3 days.

• Protect Sucraid from heat and light.

Keep Sucraid and all medicines out of the reach of children.

Manufactured by:
QOL Medical, LLC Vero Beach, FL 32963
U.S. License No. 2195

For more information, go to www.Sucraid.com or call 1-866-469-3773.

This Instructions for Use has been approved by the U.S. Food and Drug Administration.

Revised: July 2024

Instructions for Use

SUCRAID®(Su-kreid)

(sacrosidase)

oral solution

118 mL Multiple-Dose Bottle

Read this Instructions for Use before you start taking or giving SUCRAID to a child, and each time you get a refill. There may be new information. This information does not take the place of talking to your healthcare provider about your or your child’s medical condition or treatment.

Important information you need to know before taking or giving SUCRAID:

- Your healthcare provider will decide the right dose of SUCRAID for you or your child. Do notchange the dose of SUCRAID without talking to your healthcare provider.
- The dose of SUCRAID depends on body weight. Your healthcare provider will tell you how much SUCRAID you should take or give your child.
  - The dose for a child 33 pounds (15 kg) or less is 1 mL or 28 drops of SUCRAID in 2 ounces of water, milk, or infant formula.
  - The dose for a child or adult more than 33 pounds (15 kg) is 2 mL or 56 drops of SUCRAID in 4 ounces of water, milk, or infant formula.
- SUCRAID can only be dissolved with cold or room temperature water, milk, or infant formula. Do notput SUCRAID in warm or hot liquids. Do notdissolve SUCRAID with fruit juice. Do nottake or give SUCRAID with fruit juice.
- Do notwarm or heat the mixed solution before taking or giving SUCRAID.
- Measure your dose or your child’s dose of SUCRAID using the measuring scoop that comes with the SUCRAID bottle. Do notuse a kitchen teaspoon or other measuring device.
- SUCRAID should be taken or given with each meal or snack. Half of the SUCRAID dose should be taken or given at the beginning of each meal or snack. Take or give the remaining SUCRAID dose during the meal or snack.
- Do notuse the SUCRAID multiple-dose bottle if the seal has been damaged. Contact your pharmacist or healthcare provider if you cannot use the SUCRAID multiple-dose bottle.

Supplies needed to take or give SUCRAID:

- SUCRAID 118 mL multiple-dose bottle
- 1 measuring scoop (included in SUCRAID carton)
- 2 to 4 ounces of cold or room temperature water, milk, or infant formula (not included)
- Meal or snack (not included)

How to take or give SUCRAID:

Step 1:Check the expiration date on the SUCRAID bottle. Do notuse SUCRAID after the expiration date on the bottle has passed.

Step 2:Write down the date the bottle is first opened in the space provided on the bottle label.

Step 3:Each bottle of SUCRAID has a plastic screw cap that covers a dropper dispensing tip. Remove the plastic screw cap by twisting it to the left.

Step 4:Use the measuring scoop that comes in your SUCRAID carton to measure your or your child’s prescribed dose. See Figure 1. Reseal the bottle after each use by replacing and twisting the plastic screw cap to the right until tight.

Figure 1

Step 5:Mix your or your child’s prescribed dose in 2 ounces or 4 ounces of cold or room temperature water, milk, or infant formula as instructed by your healthcare provider. See Figure 2.

Figure 2

Step 6:Take or give half of the mixed solution at the beginning of each meal or snack. Take or give the remaining mixed solution during the meal or snack.

Step 7:Rinse the measuring scoop with water after each use.

Throwing away (disposal of) SUCRAID:

- Throw away (discard) the SUCRAID multiple-dose bottle and any remaining medicine in your household trash 4 weeks after first opening.

How should I store SUCRAID?

- Store the SUCRAID multiple-dose bottle in the refrigerator between 36°F to 46°F (2°C to 8°C).
- Protect SUCRAID from heat and light.

Keep SUCRAID and all medicines out of the reach of children.

Manufactured by:
QOL Medical, LLC Vero Beach, FL 32963

U.S. License No. 2195

For more information, go to www.sucraid.com or call 1-866-469-3773.

This Instructions for Use has been approved by the U.S. Food and Drug Administration. Issued: May 2022

Patient Information
SUCRAID® (Su-kreid)
(sacrosidase)
Oral Solution

What is SUCRAID?
SUCRAID is a prescription medicine for the treatment of people who were born with a lack of (deficiency) sucrase, which is part of congenital sucrase-isomaltase deficiency (CSID). It is not known if SUCRAID is safe and effective in children under 5 months of age.

Do not take or give your child SUCRAID if you or your child:

- are allergic to yeast, yeast products, glycerin (glycerol), or papain. See the end of this Patient Information leaflet for a complete list of ingredients in SUCRAID.

Before you take or give your child SUCRAID, tell your healthcare provider about all of your medical conditions, including if you or your child:

- have diabetes. SUCRAID can interact with the food in your diet and may change your blood sugar levels. Your healthcare provider will tell you if your diet or diabetes medicines need to be changed.
- are pregnant or plan to become pregnant. It is not known if SUCRAID will harm your unborn baby.
- are breastfeeding or plan to breastfeed. You and your healthcare provider should decide if you will take SUCRAID while breastfeeding.

Tell your healthcare provider about all the medicines you take,including prescription and over-the-counter medicines, vitamins, and herbal supplements.

How should I take or give SUCRAID?

- See the detailed Instructions for Use that come with this Patient Information leaflet for instructions about the right way to take or give SUCRAID.
- SUCRAID should be taken or given exactly as prescribed by your healthcare provider. Do not change the dose of SUCRAID without talking to your healthcare provider.
- SUCRAID comes in a 118-mL multiple-dose bottle or a 2-mL single-use container. Your healthcare provider will decide which type of SUCRAID is best for you to use.
- The dose of SUCRAID depends on body weight. Your healthcare provider will tell you how much SUCRAID you should take or give your child.
  - The dose for a child 33 pounds (15 kg) or less is 1 mL or 28 drops of SUCRAID in 2 ounces of water, milk, or infant formula.
  - The dose for a child or adult more than 33 pounds (15 kg) is 2 mL or 56 drops of SUCRAID in 4 ounces of water, milk, or infant formula.
- SUCRAID can only be dissolved in cold or room temperature water, milk, or infant formula. Do notput SUCRAID in warm or hot liquids.
  - Do notmix SUCRAID with fruit juice. Do nottake or give SUCRAID with fruit juice.
  - Do notwarm or heat the mixed solution before taking or giving SUCRAID.
- Measure your dose or your child’s dose of SUCRAID using the measuring scoop that comes with the SUCRAID bottle. Do notuse a kitchen teaspoon or other measuring device.
- SUCRAID should be taken or given with each meal or snack. Half of the SUCRAID dose should be taken at the beginning of each meal or snack. Take or give the remaining SUCRAID dose during the meal or snack.
- Rinse the measuring scoop with water after each use.
- SUCRAID does not break down some sugars found in foods that have starch, such as wheat, rice, and potatoes. Your healthcare provider may tell you to avoid eating foods with starch.

What are the possible side effects of SUCRAID?

SUCRAID may cause serious side effects, including:

- severe allergic reactions. Severe allergic reactions have happened in some people taking SUCRAID. Tell your healthcare provider right away or go to the nearest emergency room if you have any of the following symptoms:
  - difficulty breathing
  - wheezing
  - rash
  - swelling of the face, lips, mouth, or tongue

Your healthcare provider may need to monitor you or your child carefully when first starting treatment with SUCRAID.

The most common side effects of SUCRAID include:

- stomach (abdominal) pain
- vomiting
- nausea
- diarrhea
- constipation
- problems sleeping
- headache
- nervousness
- dehydration

These are not all of the possible side effects of SUCRAID. Call your doctor for medical advice about side effects. You may report side effects to FDA at 1-800-FDA-1088.

How should I store SUCRAID?

- SUCRAID 118 mL multiple-dose bottle
  - Store in the refrigerator between 36°F to 46°F (2°C to 8°C).
  - Throw away after 4 weeks of first opening the multiple-dose bottle.
  - Protect from heat and light.
- SUCRAID 2-mL single-use container
  - Store in the refrigerator between 36°F to 46°F (2°C to 8°C)
  - After removing from the refrigerator, the 2-mL single-use container can be stored between 59°F to 77°F (15°C to 25°C) for up to 3 days (72 hours).
  - Protect from heat and light.
- Keep SUCRAID and all medicines out of the reach of children.

General information about the safe and effective use of SUCRAID.
Medicines are sometimes prescribed for purposes other than those listed in a Patient Information leaflet. Do notuse SUCRAID for a condition for which it was not prescribed. Do notgive SUCRAID to other people, even if they have the same symptoms that you have. It may harm them.
You can ask your pharmacist or healthcare provider for information about SUCRAID that is written for health professionals.

What are the ingredients in SUCRAID?

Active ingredient:sacrosidase
Inactive ingredients:Citric acid, glycerol, sodium hydroxide, and water.

Manufactured by:
QOL Medical, LLC Vero Beach, FL 32963
U.S. License No. 2195
For more information, go to www.Sucraid.com or call 1-866-469-3773.

This Patient Package Insert has been approved by the U.S. Food and Drug Administration Revised: August 2024

118 mL Multi-dose bottle

Carton:

Bottle label:

2 mL Single-use container

Carton:

Box:

Pouch:

Single-use container: